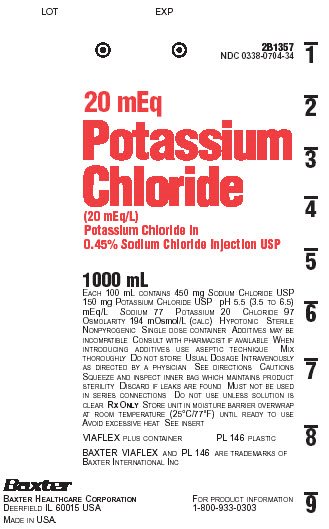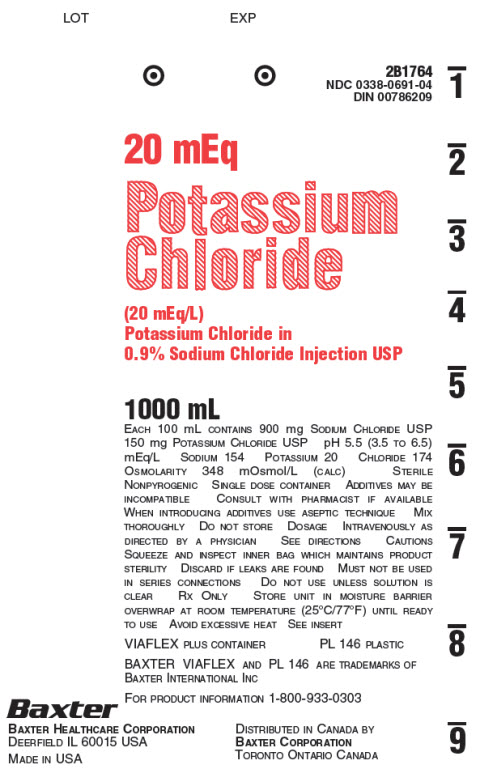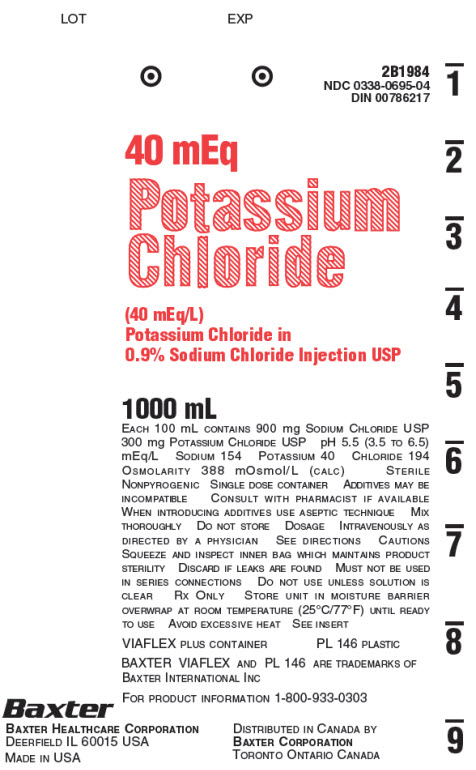 DRUG LABEL: Potassium Chloride in Sodium Chloride
NDC: 0338-0695 | Form: INJECTION, SOLUTION
Manufacturer: Baxter Healthcare Company
Category: prescription | Type: HUMAN PRESCRIPTION DRUG LABEL
Date: 20190111

ACTIVE INGREDIENTS: SODIUM CHLORIDE 900 mg/100 mL; POTASSIUM CHLORIDE 300 mg/100 mL
INACTIVE INGREDIENTS: WATER

Potassium Chloride in Sodium Chloride Injection, USP
in Plastic Container
VIAFLEX Plus Container

DESCRIPTION

Potassium Chloride in Sodium Chloride Injection, USP is a sterile, nonpyrogenic, solution for fluid and electrolyte replenishment in a single dose container for intravenous administration. It contains no antimicrobial agents. Composition, osmolarity, pH and ionic concentration are shown in Table 1.

Table 1 | Size (mL) | Composition (g/L) |  | [Normal physiologic osmolarity range is approximately 280 to 310 mOsmol/L. Administration of substantially hypertonic solutions (≥ 600 mOsmol/L) may cause vein damage.] Osmolarity (mOsmol/L) (Calc.) | pH | Ionic Concentration (mEq/L)
Table 1 | Size (mL) | Sodium Chloride, USP (NaCl) | Potassium Chloride, USP (KCl) | [Normal physiologic osmolarity range is approximately 280 to 310 mOsmol/L. Administration of substantially hypertonic solutions (≥ 600 mOsmol/L) may cause vein damage.] Osmolarity (mOsmol/L) (Calc.) | pH | Sodium | Potassium | Chloride
20 mEq/L Potassium Chloride in 0.45% Sodium Chloride Injection, USP | 1000 | 4.5 | 1.5 | 194 | 5.5; (3.5 to 6.5) | 77 | 20 | 97
20 mEq/L Potassium Chloride in 0.9% Sodium Chloride Injection, USP | 1000 | 9 | 1.5 | 348 | 5.5; (3.5 to 6.5) | 154 | 20 | 174
40 mEq/L Potassium Chloride in 0.9% Sodium Chloride Injection, USP | 1000 | 9 | 3 | 388 | 5.5; (3.5 to 6.5) | 154 | 40 | 194

The VIAFLEX Plus plastic container is fabricated from a specially formulated polyvinyl chloride (PL 146 Plastic). VIAFLEX Plus on the container indicates the presence of a drug additive in a drug vehicle. The VIAFLEX Plus plastic container system utilizes the same container as the VIAFLEX plastic container system. The amount of water that can permeate from inside the container into the overwrap is insufficient to affect the solution significantly. Solutions in contact with the plastic container can leach out certain of its chemical components in very small amounts within the expiration period, e.g., di-2-ethylhexyl phthalate (DEHP), up to 5 parts per million. However, the safety of the plastic has been confirmed in tests in animals according to USP biological tests for plastic containers as well as by tissue culture toxicity studies.

CLINICAL PHARMACOLOGY

Potassium Chloride in Sodium Chloride Injection, USP has value as a source of water and electrolytes. It is capable of inducing diuresis depending on the clinical condition of the patient.

INDICATIONS AND USAGE

Potassium Chloride in Sodium Chloride Injection, USP is indicated as a source of water and electrolytes.

CONTRAINDICATIONS

Potassium Chloride in Sodium Chloride Injection, USP is contraindicated in patients with:

- Known hypersensitivity to potassium chloride and/or sodium chloride (see WARNINGS).
- Clinically significant hyperkalemia (see WARNINGS).

WARNINGS

Hypersensitivity

Hypersensitivity and infusion reactions, including anaphylaxis and chills, have been reported with products containing potassium chloride and sodium chloride. Stop the infusion immediately if signs or symptoms of a hypersensitivity or infusion reaction develops. Appropriate therapeutic countermeasures must be instituted as clinically indicated.

Electrolyte Imbalances

Hyperkalemia

Potassium-containing solutions, including Potassium Chloride in Sodium Chloride Injection, USP may increase the risk of hyperkalemia. Hyperkalemia can be asymptomatic and manifest only by increased serum potassium concentrations and/or characteristic electrocardiographic (ECG) changes. Cardiac conduction disorders (including complete heart block) and other cardiac arrhythmias, some fatal, can develop at any time during hyperkalemia. Continuous electrocardiogram (ECG) monitoring may be necessary to aid in the detection of cardiac arrhythmias due to hyperkalemia (see ADVERSE REACTIONS).

To avoid life threatening hyperkalemia, do not administer Potassium Chloride in Sodium Chloride Injection, USP as an intravenous push (i.e., intravenous injection manually with a syringe connected to the intravenous access) without a quantitative infusion device.

Patients at increased risk of developing hyperkalemia and cardiac arrhythmias include those:

- with conditions predisposing to hyperkalemia and/or associated with increased sensitivity to potassium, such as patients with severe renal impairment, acute dehydration, extensive tissue injury or burns, certain cardiac disorders such as congestive heart failure or atrioventricular (AV) block (especially if they receive digoxin).
- who are at risk of experiencing hyperosmolality, acidosis, or undergoing correction of alkalosis (conditions associated with a shift of potassium from intracellular to extracellular space).
- treated concurrently or recently with agents or products that can cause or increase the risk of hyperkalemia (see DRUG INTERACTIONS).
- with cardiac arrhythmias.

Avoid use of Potassium Chloride in Sodium Chloride Injection, USP in patients with, or at risk for, hyperkalemia. If use cannot be avoided, use a product with a low amount of potassium chloride, infuse slowly and monitor serum potassium concentrations and ECGs.

Hypernatremia and Hyperchloremia

Electrolyte imbalances such as hypernatremia, hyperchloremia, and metabolic acidosis may occur with Potassium Chloride in Sodium Chloride Injection, USP.

Conditions that may increase the risk of hypernatremia, fluid overload and edema (central and peripheral), include patients with: primary hyperaldosteronism; secondary hyperaldosteronism associated with, for example, hypertension, congestive heart failure, liver disease (including cirrhosis), renal disease (including renal artery stenosis, nephrosclerosis); and pre-eclampsia.

Certain medications, such as corticosteroids or corticotropin, may also increase risk of sodium and fluid retention, see DRUG INTERACTIONS.

Avoid Potassium Chloride in Sodium Chloride Injection, USP in patients with, or at risk for, hypernatremia or hyperchloremia. If use cannot be avoided, monitor serum sodium and chloride concentrations and acid-base balance.

Rapid correction of hypernatremia is potentially dangerous with risk of serious neurologic complications. Excessively rapid correction of hypernatremia is also associated with a risk for serious neurologic complications such as osmotic demyelination syndrome (ODS) with risk of seizures and cerebral edema.

Hyponatremia

Potassium Chloride in Sodium Chloride Injection, USP may cause hyponatremia. Hyponatremia can lead to acute hyponatremic encephalopathy characterized by headache, nausea, seizures, lethargy, and vomiting. Patients with brain edema are at particular risk of severe, irreversible and life-threatening brain injury.

The risk of hospital-acquired hyponatremia is increased in patients with cardiac or pulmonary failure, and in patients with non-osmotic vasopressin release (including SIADH) treated with high volume of hypotonic Potassium Chloride in Sodium Chloride Injection, USP.

The risk for hyponatremia is increased in pediatric patients, elderly patients, postoperative patients, those with psychogenic polydipsia, and in patients treated with medications that increase the risk of hyponatremia (such as diuretics, certain antiepileptic and psychotropic medications). See DRUG INTERACTIONS.

Patients at increased risk for developing complications of hyponatremia such as hyponatremic encephalopathy, include pediatric patients, women (in particular, premenopausal women), patients with hypoxemia, and patients with underlying central nervous system disease. Avoid Potassium Chloride in Sodium Chloride Injection, USP in patients with or at risk for hyponatremia. If use cannot be avoided, monitor serum sodium concentrations.

Rapid correction of hyponatremia is potentially dangerous with risk of serious neurologic complications. Brain adaptations reducing risk of cerebral edema make the brain vulnerable to injury when chronic hyponatremia is too rapidly corrected, which is known as osmotic demyelination syndrome (ODS). To avoid complications, monitor serum sodium and chloride concentrations, fluid status, acid-base balance, and signs of neurologic complications.

Fluid Overload

Depending on the volume and rate of infusion, and the patient’s underlying clinical condition, the intravenous administration of Potassium Chloride in Sodium Chloride Injection, USP can cause electrolyte disturbances such as overhydration/hypervolemia and congested states including central (e.g., pulmonary edema) and peripheral edema.

Avoid Potassium Chloride in Sodium Chloride Injection, USP in patients with or at risk for fluid and/or solute overloading. If use cannot be avoided, monitor fluid balance, electrolyte concentrations and acid base balance as needed and especially during prolonged use.

PRECAUTIONS

Patients with Severe Renal Impairment

Administration of sodium and potassium in patients with or at risk of severe renal impairment, may result in hypernatremia, hyperkalemia and/or fluid overload (see WARNINGS). Avoid Potassium Chloride in Sodium Chloride Injection, USP in patients with severe renal impairment. If use cannot be avoided, monitor patients with severe renal impairment for development of these adverse reactions.

Drug Interactions

Lithium
Renal sodium and lithium clearance may be increased during administration of Potassium Chloride in Sodium Chloride Injection, USP and result in decreased lithium concentrations. Monitor serum lithium concentrations during concomitant use.
Other Products that Cause Hyperkalemia
Administration of Potassium Chloride in Sodium Chloride Injection, USP in patients treated concurrently or recently with products that are associated with hyperkalemia increases the risk of severe and potentially fatal hyperkalemia, in particular in the presence of other risk factors for hyperkalemia. Avoid use of Potassium Chloride in Sodium Chloride Injection, USP in patients receiving such products (e.g., potassium sparing diuretics, angiotensin-converting enzyme inhibitors, angiotensin receptor blockers, or the immunosuppressants cyclosporine and tacrolimus). If use cannot be avoided, monitor serum potassium concentrations.
Other Products that Affect Fluid and/or Electrolyte Balance
Administration of Potassium Chloride in Sodium Chloride Injection, USP in patients treated concomitantly with medications associated with sodium and fluid retention may increase the risk of hypernatremia and volume overload. Avoid use of Potassium Chloride in Sodium Chloride Injection, USP in patients receiving such products, such as corticosteroids or corticotropin. If use cannot be avoided, monitor serum electrolytes, fluid balance, and acid-base balance.
Other Drugs that Increase the Risk of Hyponatremia
Administration of Potassium Chloride in Sodium Chloride Injection, USP in patients treated concomitantly with medications associated with hyponatremia may increase the risk of developing hyponatremia.
Avoid use of Potassium Chloride in Sodium Chloride Injection, USP in patients receiving products, such as diuretics, and certain antiepileptic and psychotropic medications. Drugs that increase the vasopressin effect reduce renal electrolyte free water excretion and may also increase the risk of hyponatremia following treatment with intravenous fluids. If use cannot be avoided, monitor serum sodium concentrations.

Pregnancy

There are no adequate and well controlled studies from the use of Potassium Chloride in Sodium Chloride Injection, USP in pregnant or lactating women and animal reproduction studies have not been conducted with this drug. Therefore, it is also not known whether Potassium Chloride in Sodium Chloride Injection, USP can cause fetal harm when administered to a pregnant woman or can affect reproduction capacity. Potassium Chloride in Sodium Chloride Injection, USP should be given to a pregnant woman only if the potential benefit justifies the potential risk to the fetus.

Nursing Mothers

It is not known whether this drug is excreted in human milk. Because many drugs are excreted in human milk, caution should be exercised when Potassium Chloride in Sodium Chloride Injection, USP is administered to a nursing mother.

Pediatric Use

The use of Potassium Chloride in Sodium Chloride Injection, USP in pediatric patients is based on clinical practice. (See DOSAGE AND ADMINISTRATION). Safety and effectiveness of Potassium Chloride in Sodium Chloride Injection, USP in pediatric patients have not been established by adequate and well-controlled studies.

Pediatric patients are at increased risk of developing hyponatremia as well as for developing encephalopathy as a complication of hyponatremia (see WARNINGS).

Geriatric Use

Geriatric patients are at increased risk of developing electrolyte imbalances. Potassium Chloride in Sodium Chloride Injection, USP is known to be substantially excreted by the kidney, and the risk of toxic reactions to this drug may be greater in patients with impaired renal function. Therefore, dose selection for an elderly patient should be cautious, usually starting at the low end of the dosing range, reflecting the greater frequency of decreased hepatic, renal, or cardiac function, and of concomitant disease or other drug therapy. Consider monitoring renal function in elderly patients.

ADVERSE REACTIONS

The following adverse reactions associated with the use of Potassium Chloride in Sodium Chloride Injection, USP were identified in clinical trials or postmarketing reports. Because postmarketing reactions were reported voluntarily from a population of uncertain size, it is not always possible to estimate their frequency, reliably, or to establish a causal relationship to drug exposure.
General disorders and administration site conditions: Chills, and infusion site pain.
Hypersensitivity reactions: generalized papules and erythema, rash, fever, vomiting, hypertension, tachycardia.
Metabolism and nutrition disorders: Hyperkalemia, hyponatremia, hypernatremia, hyperchloremia acidosis, fluid overload.
Cardiac disorders: Cardiac arrest as a manifestation of rapid intravenous administration and/or of hyperkalemia.
Nervous System Disorders: Hyponatremic encephalopathy.

If an adverse reaction does occur, discontinue the infusion, evaluate the patient, institute appropriate therapeutic countermeasures and save the remainder of the fluid for examination if deemed necessary.

OVERDOSAGE

An increased infusion rate of Potassium Chloride in Sodium Chloride Injection, USP can cause:

- hyperkalemia, manifestations may include disturbances in cardiac conduction and arrhythmias, including bradycardia, heart block, asystole, ventricular tachycardia, ventricular fibrillation.
The presence of any ECG findings that are suspected to be caused by hyperkalemia should be considered a medical emergency.
If hyperkalemia is present or suspected, discontinue the infusion immediately and institute close ECG, laboratory and other monitoring and, as necessary, corrective therapy to reduce serum potassium concentrations.
Muscle weakness (up to and including muscular and respiratory paralysis, paresthesia of extremities) may occur as a complication of hyperkalemia.
- hyponatremia, manifestations may include seizures, coma, cerebral edema and death).
- hypernatremia, especially in patients with severe renal impairment.
- hypotension.
- gastrointestinal symptoms (ileus, nausea, vomiting, abdominal pain).
- fluid overload (which can lead to central and/or peripheral edema). See WARNINGS and ADVERSE REACTIONS.

When assessing an overdose, any additives in the solution must also be considered. The effects of an overdose may require immediate medical attention and treatment. Interventions include discontinuation of Potassium Chloride in Sodium Chloride Injection, USP administration, dose reduction, and other measures as indicated for the specific clinical constellation (e.g., monitoring of fluid balance, electrolyte concentrations and acid base balance).

DOSAGE AND ADMINISTRATION

Important Administration Instructions
2. Potassium Chloride in Sodium Chloride Injection, USP is intended for intravenous infusion using sterile equipment.
3. To avoid life threatening hyperkalemia, do not administer Potassium Chloride in Sodium Chloride Injection, USP as an intravenous push (i.e., intravenous injection manually with a syringe connected to the intravenous access) without a quantitative infusion device (see WARNINGS).
4. Do not connect flexible plastic containers in series in order to avoid air embolism due to possible residual air contained in the primary container.
5. Set the vent to the closed position on a vented intravenous administration set to prevent air embolism.
6. Use a dedicated line without any connections to avoid air embolism.
7. Do not pressurize intravenous solutions contained in flexible plastic containers to increase flow rates in order to avoid air embolism due to incomplete evacuation of residual air in the container.
8. The choice of a central or peripheral venous route of infusion should depend on the osmolarity of the final infusate. Solutions with osmolarity of greater than or equal to approximately 900 mOsm/L must be infused through a central catheter.
9. Prior to infusion, visually inspect the solution for particulate matter and discoloration. The solution should be clear and there should be no precipitates. Do not administer unless solution is clear and container is undamaged.
10. Use of final filter is recommended during administration of all parenteral solutions, where possible.
Dosing Information
The choice of the specific potassium chloride and sodium chloride formulation, dosage, volume, rate and duration of administration is dependent upon the age, weight and clinical and metabolic condition of the patient and concomitant therapy, and administration should be determined by a physician experienced in intravenous fluid therapy.
Additional electrolyte supplementation may be indicated according to the clinical needs of the patient. Additives can be introduced to the container; however, some additives may be incompatible. Evaluate all additions to the plastic container for compatibility and stability of the resulting preparation. Consult with a pharmacist, if available.
If, in the informed judgment of the physician, it is deemed advisable to introduce additives, use aseptic technique. After addition, if there is a discoloration and/or the appearance of precipitates, insoluble complexes or crystals, do not use. Mix thoroughly when additives have been introduced. Do not store solutions containing additives. Discard any unused portion.
Rapid correction of hyponatremia and hypernatremia is potentially dangerous (risk of serious neurologic complications). To avoid complications such as osmotic demyelination syndrome (ODS) during administration, follow the important administration instructions, monitor serum sodium and chloride concentrations, fluid status, acid-base balance, and signs of neurologic complications.

HOW SUPPLIED

Potassium Chloride in Sodium Chloride Injection, USP in VIAFLEX Plus Plastic Container is available as follows:

Code | Size (mL) | NDC | Product Name
2B1357 | 1000 | 0338-0704-34 | 20 mEq/L Potassium Chloride in 0.45% Sodium Chloride Injection, USP
2B1764 | 1000 | 0338-0691-04 | 20 mEq/L Potassium Chloride in 0.9% Sodium Chloride Injection, USP
2B1984 | 1000 | 0338-0695-04 | 40 mEq/L Potassium Chloride in 0.9% Sodium Chloride Injection, USP

Exposure of pharmaceutical products to heat should be minimized. Avoid excessive heat. It is recommended the product be stored between 20ºC to 25°C (68º F to 77°F). [See USP controlled room temperature.]; brief exposure up to 40° C (104° F) does not adversely affect the product.

DIRECTIONS FOR USE OF VIAFLEX PLUS PLASTIC CONTAINER

For information on risk of air embolism – see PRECAUTIONS.

To Open

Tear overwrap down side at slit and remove solution container. Visually inspect the container. If the outlet port protector is damaged, detached, or not present, discard container as solution path sterility may be impaired. Some opacity of the plastic due to moisture absorption during the sterilization process may be observed. This is normal and does not affect the solution quality or safety. The opacity will diminish gradually. Check for minute leaks by squeezing inner bag firmly. If leaks are found, discard solution as sterility may be impaired. If supplemental medication is desired, follow directions below.

Preparation for Administration

1. Suspend container from eyelet support.
2. Remove plastic protector from outlet port at bottom of container.
3. Attach administration set. Refer to complete directions accompanying set.

To Add Medication

Warning: Additives may be incompatible.

To add medication before solution administration

1. Prepare medication site.
2. Using syringe with 19 to 22 gauge needle, puncture resealable medication port and inject.
3. Mix solution and medication thoroughly. For high density medication such as potassium chloride, squeeze ports while ports are upright and mix thoroughly.

To add medication during solution administration

1. Close clamp on the set.
2. Prepare medication site.
3. Using syringe with 19 to 22 gauge needle, puncture resealable medication port and inject.
4. Remove container from IV pole and/or turn to an upright position.
5. Evacuate both ports by squeezing them while container is in the upright position.
6. Mix solution and medication thoroughly.
7. Return container to in use position and continue administration.

Baxter Healthcare Corporation
Deerfield, IL 60015 USA

Printed in USA

07-19-78-210

Rev. January 2019

Baxter, and Viaflex are trademarks of Baxter International Inc.

For Product Information
1-800-933-0303

PACKAGE LABELING - PRINCIPLE DISPLAY PANEL

Container Label

Container Label

LOT EXP

2B1357
NDC 0338-0704-34

20 mEq
Potassium Chloride
(20 mEq/L)
Potassium Chloride in
0.45% Sodium Chloride Injection USP

1000 mL

EACH 100 mL CONTAINS 450 mg SODIUM CHLORIDE USP
150 mg POTASSIUM CHLORIDE USP pH 5.5 (3.5 TO 6.5)
mEq/L SODIUM 77 POTASSIUM 20 CHLORIDE 97

OSMOLARITY 194 mOsmol/L (CALC) HYPOTONIC STERILE
NONPYROGENIC SINGLE DOSE CONTAINER ADDITIVES MAY BE
INCOMPATIBLE CONSULT WITH PHARMACIST IF AVAILABLE WHEN
INTRODUCING ADDITIVES USE ASEPTIC TECHNIQUE MIX
THOROUGHLY DO NOT STORE USUAL DOSAGE INTRAVENOUSLY
AS DIRECTED BY A PHYSICIAN SEE DIRECTIONS CAUTIONS
SQUEEZE AND INSPECT INNER BAG WHICH MAINTAINS PRODUCT
STERILITY DISCARD IF LEAKS ARE FOUND MUST NOT BE USED
IN SERIES CONNECTIONS DO NOT USE UNLESS SOLUTION IS
CLEAR RX ONLY STORE UNIT IN MOISTURE BARRIER OVERWRAP
AT ROOM TEMPERATURE (25°C/77°F) UNTIL READY TO USE
AVOID EXCESSIVE HEAT SEE INSERT

VIAFLEX PLUS CONTAINER PL 146 PLASTIC

BAXTER VIAFLEX AND PL 146 ARE TRADEMARKS OF
BAXTER INTERNATIONAL INC

Baxter
BAXTER HEALTHCARE CORPORATION
DEERFIELD IL 60015 USA

MADE IN USA

FOR PRODUCT INFORMATION
1-800-933-0303

Container Label

LOT EXP

2B1764
NDC 0338-0691-04
DIN 00786209

1000 mL

EACH 100 mL CONTAINS 900 mg SODIUM CHLORIDE USP
150 mg POTASSIUM CHLORIDE USP pH 5.5 (3.5 TO 6.5)
mEq/L SODIUM 154 POTASSIUM 20 CHLORIDE 174
OSMOLARITY 348 mOsmol/L (CALC) STERILE
NONPYROGENIC SINGLE DOSE CONTAINER ADDITIVES MAY BE
INCOMPATIBLE CONSULT WITH PHARMACIST IF AVAILABLE
WHEN INTRODUCING ADDITIVES USE ASEPTIC TECHNIQUE MIX
THOROUGHLY DO NOT STORE DOSAGE INTRAVENOUSLY AS
DIRECTED BY A PHYSICIAN SEE DIRECTIONS CAUTIONS
SQUEEZE AND INSPECT INNER BAG WHICH MAINTAINS PRODUCT
STERILITY DISCARD IF LEAKS ARE FOUND MUST NOT BE USED
IN SERIES CONNECTIONS DO NOT USE UNLESS SOLUTION IS
CLEAR RX ONLY STORE UNIT IN MOISTURE BARRIER
OVERWRAP AT ROOM TEMPERATURE (25°C/77°F) UNTIL READY
TO USE AVOID EXCESSIVE HEAT SEE INSERT

VIAFLEX PLUS CONTAINER PL 146 PLASTIC
BAXTER VIAFLEX AND PL 146 ARE TRADEMARKS OF
BAXTER INTERNATIONAL INC

FOR PRODUCT INFORMATION 1-800-933-0303

Baxter

BAXTER HEALTHCARE CORPORATION
DEERFIELD IL 60015 USA
MADE IN USA

DISTRIBUTED IN CANADA BY
BAXTER CORPORATION
TORONTO ONTARIO CANADA

Container Label

LOT EXP

2B1984
NDC 0338-0695-04
DIN 00786217

1000 mL

EACH 100 mL CONTAINS 900 mg SODIUM CHLORIDE USP
300 mg POTASSIUM CHLORIDE USP pH 5.5 (3.5 TO 6.5)
mEq/L SODIUM 154 POTASSIUM 40 CHLORIDE 194
OSMOLARITY 388 mOsmol/L (CALC) STERILE
NONPYROGENIC SINGLE DOSE CONTAINER ADDITIVES MAY BE
INCOMPATIBLE CONSULT WITH PHARMACIST IF AVAILABLE
WHEN INTRODUCING ADDITIVES USE ASEPTIC TECHNIQUE MIX
THOROUGHLY DO NOT STORE DOSAGE INTRAVENOUSLY AS
DIRECTED BY A PHYSICIAN SEE DIRECTIONS CAUTIONS
SQUEEZE AND INSPECT INNER BAG WHICH MAINTAINS PRODUCT
STERILITY DISCARD IF LEAKS ARE FOUND MUST NOT BE USED
IN SERIES CONNECTIONS DO NOT USE UNLESS SOLUTION IS
CLEAR RX ONLY STORE UNIT IN MOISTURE BARRIER
OVERWRAP AT ROOM TEMPERATURE (25°C/77°F) UNTIL READY
TO USE AVOID EXCESSIVE HEAT SEE INSERT

VIAFLEX PLUS CONTAINER PL 146 PLASTIC
BAXTER VIAFLEX AND PL 146 ARE TRADEMARKS OF
BAXTER INTERNATIONAL INC

FOR PRODUCT INFORMATION 1-800-933-0303

Baxter

BAXTER HEALTHCARE CORPORATION
DEERFIELD IL 60015 USA
MADE IN USA

DISTRIBUTED IN CANADA BY
BAXTER CORPORATION

TORONTO ONTARIO CANADA